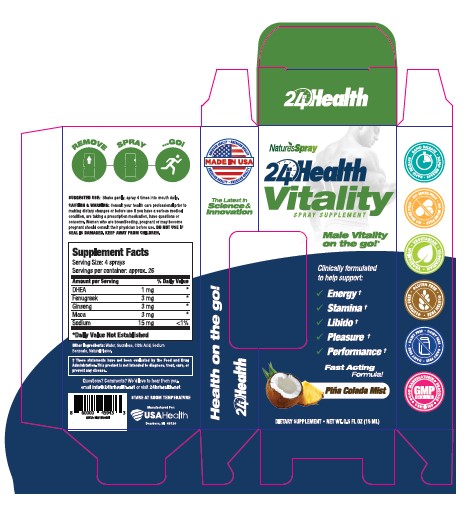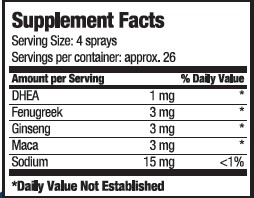 DRUG LABEL: 24hr Health Vitality
NDC: 80893-005 | Form: SPRAY
Manufacturer: USA Health
Category: other | Type: Dietary Supplement
Date: 20201106

ACTIVE INGREDIENTS: PRASTERONE 1 mg/15 mL; SODIUM 15 mg/15 mL; LEPIDIUM MEYENII ROOT 3 mg/15 mL; FENUGREEK SEED 3 mg/15 mL; ASIAN GINSENG 3 mg/15 mL
INACTIVE INGREDIENTS: water; SUCRALOSE; CITRIC ACID MONOHYDRATE; SODIUM BENZOATE

24hr Health Vitality

Purpose

Clinically formulated to help support:

- Energy
- Stamina
- Libido
- Pleasure
- Performance

Precaution

Consult your health care professional prior to making dietary changes or before use if you have a serious medical condition, are taking a prescription medicine, have questions or concerns.

Warnings

Women who are breastfeeding, pregnant, or may become pregnant should consult their physician before use.

Safe Handling

Do not use if seal is damaged. Keep away from children.

Dosage

Shake gently. Spray 4 times into mouth daily.